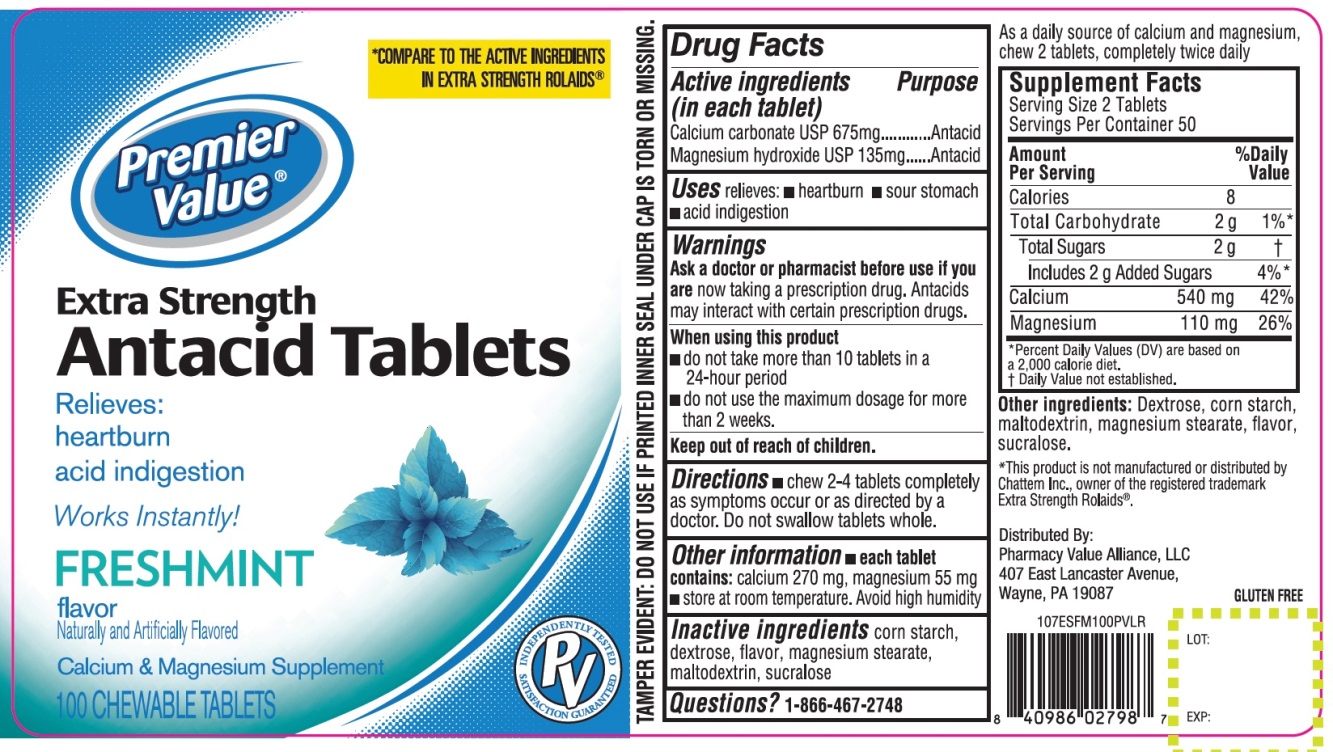 DRUG LABEL: Premier Value Extra Strength
NDC: 68016-678 | Form: TABLET, CHEWABLE
Manufacturer: CHAIN DRUG CONSORTIUM, LLC
Category: otc | Type: HUMAN OTC DRUG LABEL
Date: 20241025

ACTIVE INGREDIENTS: CALCIUM CARBONATE 675 mg/1 1; MAGNESIUM HYDROXIDE 135 mg/1 1
INACTIVE INGREDIENTS: STARCH, CORN; DEXTROSE, UNSPECIFIED FORM; MAGNESIUM STEARATE; MALTODEXTRIN; SUCRALOSE

Premier Value® Extra Strength Antacid Tablets Freshmint Flavor

Drug Facts

Active ingredients (in each tablet)

Calcium Carbonate USP 675 mg
Magnesium hydroxide USP 135 mg

Purpose

Antacid

Antacid

Uses

relieves:

- heartburn
- sour stomach
- acid indigestion

Warnings

Ask a doctor or pharmacist before use if you are

now taking a prescription drug. Antacids may interact with certain prescription drugs.

When using this product

- do not take more than 10 tablets in a 24-hour period
- do not use the maximum dosage for more than 2 weeks.

Directions

- chew 2-4 tablets completely as symptoms occur or as directed by a doctor. Do not swallow tablet whole.

Other information

- each tablet contains: calcium 270 mg, magnesium 55 mg
- store room temperature
- Avoid high humidity.

DO NOT USE IF PRINTED INNER SEAL IS BROKEN OR MISSING

CALCIUM SUPPLEMENT

USES

As a daily source of calcium and magnesium, chew 2 tablets, completely twice daily

Supplement Facts

Serving Size: 2 Tablets

Servings Per Container: 50

Amount Per Serving | % Daily Value
Calories 8
Total Carbohydrate 2g | 1%
Total Sugars 2g | †
Includes 2 g Added Sugar | 4%
Calcium 540 mg | 42%
Magnesium 110 mg | 26%

*Percent Daily Values (DV) are based on a 2,000 calories diet.

†Daily Value not established.

Inactive ingredients

corn starch, dextrose, flavor, magnesium stearate, maltodextrin, sucralose.

Questions?

1-866-467-2748

PRINCIPAL DISPLAY PANEL

Premier Value®

NDC# 68016-678-00

COMPARE TO ACTIVE INGREDIENTS IN ROLAIDS® EXTRA STRENGTH*

Extra Strength

Antacid Tablets

Freshmint Flavor

Relieves:

- Heartburn
- Acid Indigestion

Antacid/Calcium Supplement

100 CHEWABLE TABLETS

GLUTEN FREE

TAMPER EVIDENT: DO NOT USE IF PRINTED INNER SEAL IS BROKEN OR MISSING

*This product is not manufactured or distributed by Chattem Inc., owner of the registered trademark Extra Strength Rolaids®

Distributed by:

Pharmacy Value Alliance, LLC

407 East Lancaster Avenue,

Wayne, PA 19087